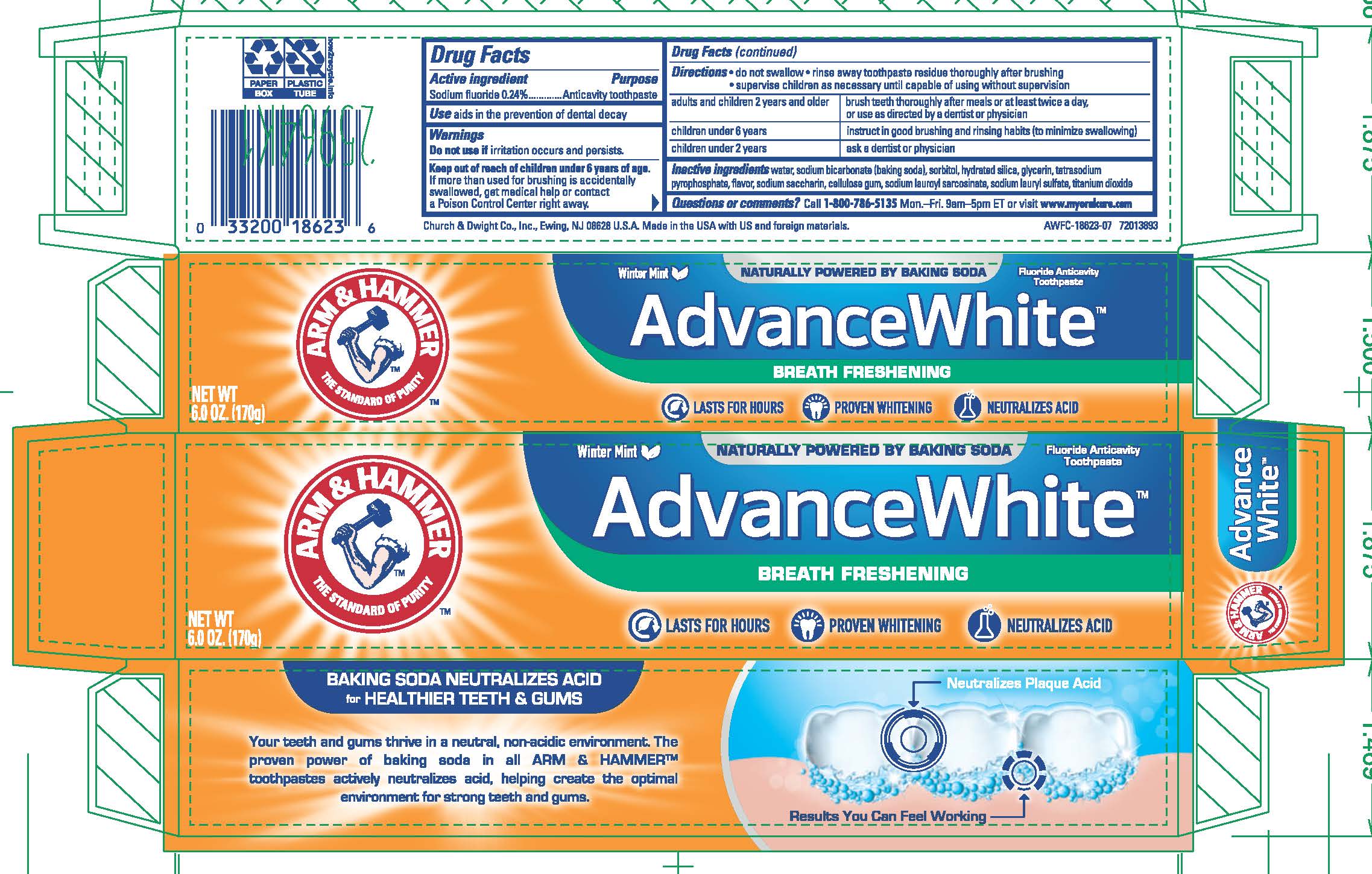 DRUG LABEL: Advance White
NDC: 10237-656 | Form: PASTE, DENTIFRICE
Manufacturer: Church & Dwight Co., Inc.
Category: otc | Type: HUMAN OTC DRUG LABEL
Date: 20241120

ACTIVE INGREDIENTS: SODIUM FLUORIDE 2.4 mg/1 g
INACTIVE INGREDIENTS: WATER; SODIUM BICARBONATE; SORBITOL; HYDRATED SILICA; GLYCERIN; SODIUM PYROPHOSPHATE; SACCHARIN SODIUM; CARBOXYMETHYLCELLULOSE SODIUM, UNSPECIFIED; SODIUM LAUROYL SARCOSINATE; SODIUM LAURYL SULFATE; TITANIUM DIOXIDE

Advance White Tartar Control Breath Freshening

Active ingredients
Sodium fluoride (0.24%)

Purpose
Anticavity toothpaste

INDICATIONS AND USAGE

Use aids in the prevention of dental decay

Warning

Keep out of reach of children under 6 years of age.

Keep out of reach of children under 6 years of age.

If more than used for brushing is accidentally swallowed, get medical help or contact a Poison Control Center right away.

DOSAGE AND ADMINISTRATION

Directions do not swallow supervise children as necessary until capable of using without supervision
adults and children 2 years and older brush teeth throughly after meals or at least twice a day, or use as directed by a dentist or physician
children under 6 years instruct in good rushing and rinsing habits (to minimize swallowing)
children under 2 years consult a dentist or physician

INACTIVE INGREDIENT

Inactive ingredients water, sodium bicarbonate (baking soda), sorbitol, hydrated silica, glycerin, tetrasodium pyrophosphate, flavor, sodium saccharin, cellulose gum, sodium lauroyl sarcosinate, sodium lauryl sulfate, titanium dioxide

Questions or comments? Call 1-800-786-5135Monday-Friday 9am-5pm ET or visit www.myoralcare.com

Principal Display Panel

ARM AND HAMMER

The Standard of Purity

Winter Mint NATURALLY POWERED BY BAKING SODA Fluoride Anticavity Toothpaste

AdvanceWhite

BREATH FRESHENING

LASTS FOR HOURS PROVEN WHITENING NEUTRALIZES ACID

NET WT. 6.0OZ. (170g)

DA2012158_AWFC-18623-07